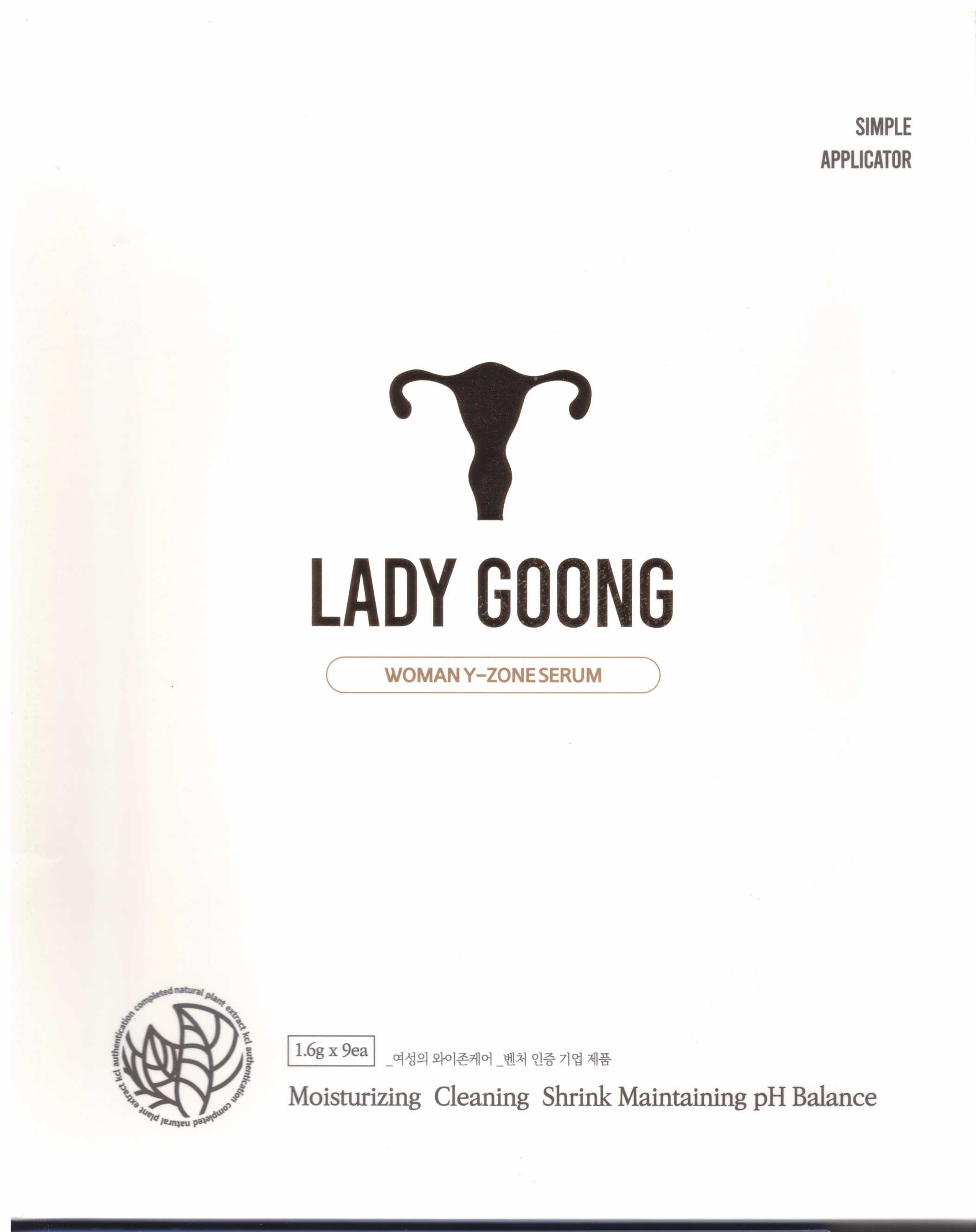 DRUG LABEL: LADY GOONG
NDC: 80766-0005 | Form: LIQUID
Manufacturer: Lady House Co., Ltd.
Category: otc | Type: HUMAN OTC DRUG LABEL
Date: 20201021

ACTIVE INGREDIENTS: ETHYLHEXYLGLYCERIN 1 g/100 g
INACTIVE INGREDIENTS: WATER

Drug Facts

ACTIVE INGREDIENT

ethylhexylglycerin

PURPOSE

moisturizing cleaning shrink maintaining pH balance

KEEP OUT OF REACH OF THE CHILDREN

INDICATIONS AND USAGE

apply proper amount to the vaginal

WARNINGS

■ For external use only.

■ Do not use in eyes.

■ lf swallowed, get medical help promptly.

■ Stop use, ask doctor lf irritation occurs.

■ Keep out of reach of children.

DOSAGE AND ADMINISTRATION

for vaginal use only

INACTIVE INGREDIENT

water, sorbitol, etc